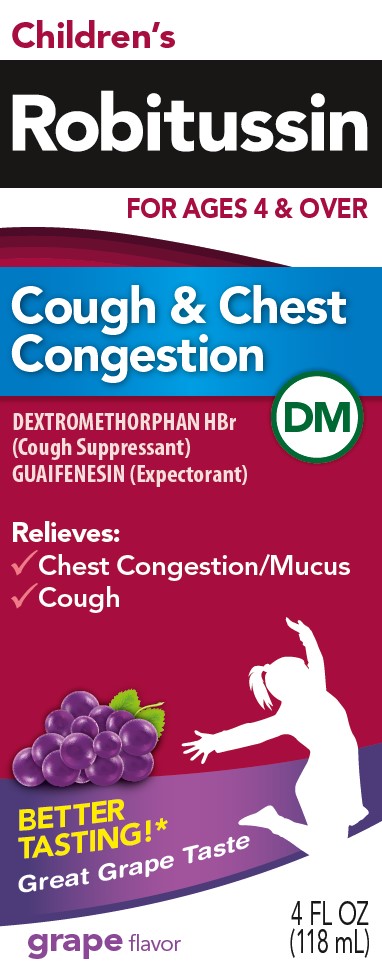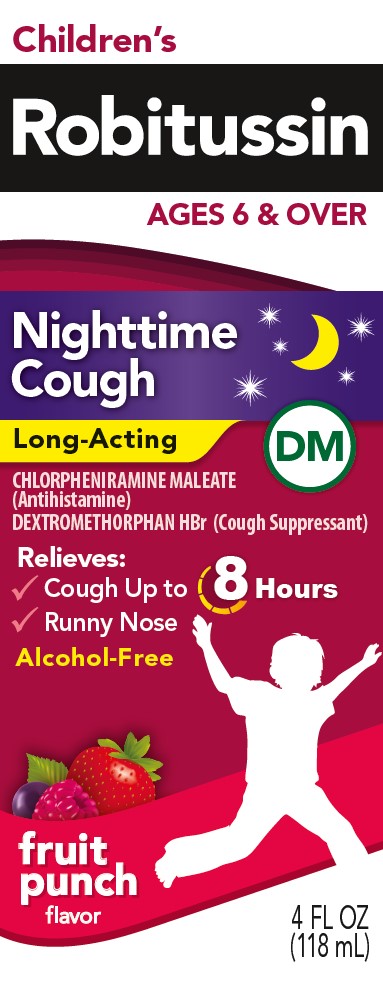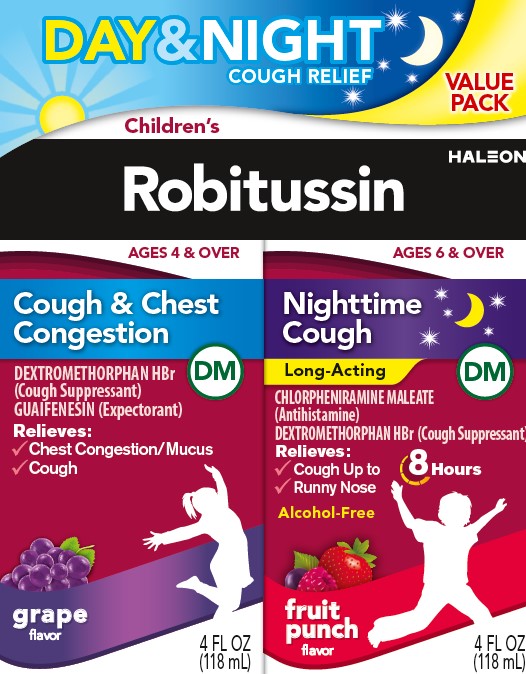 DRUG LABEL: Robitussin

NDC: 0031-2099 | Form: KIT | Route: ORAL
Manufacturer: Haleon US Holdings LLC
Category: otc | Type: HUMAN OTC DRUG LABEL
Date: 20251015

ACTIVE INGREDIENTS: DEXTROMETHORPHAN HYDROBROMIDE 20 mg/20 mL; GUAIFENESIN 200 mg/20 mL; CHLORPHENIRAMINE MALEATE 2 mg/10 mL; DEXTROMETHORPHAN HYDROBROMIDE 15 mg/10 mL
INACTIVE INGREDIENTS: ANHYDROUS CITRIC ACID; CARBOXYMETHYLCELLULOSE SODIUM, UNSPECIFIED; FD&C BLUE NO. 1; FD&C RED NO. 40; GLYCERIN; DEXTROSE, UNSPECIFIED FORM; POLYETHYLENE GLYCOL, UNSPECIFIED; PROPYLENE GLYCOL; WATER; SODIUM BENZOATE; SODIUM CITRATE, UNSPECIFIED FORM; SODIUM GLUCONATE; SUCRALOSE; XANTHAN GUM; ANHYDROUS CITRIC ACID; FD&C RED NO. 40; GLYCERIN; LACTIC ACID, UNSPECIFIED FORM; PROPYLENE GLYCOL; WATER; SODIUM BENZOATE; SODIUM CITRATE, UNSPECIFIED FORM; SORBITOL; SUCRALOSE

Drug Facts

Active ingredients (in each 20 mL)– Children’s Robitussin Cough & Chest Congestion DM

Dextromethorphan HBr 20 mg

Guaifenesin 200 mg

Purposes– Children’s Robitussin Cough & Chest Congestion DM

Cough Suppressant

Expectorant

Uses– Children’s Robitussin Cough & Chest Congestion DM

- temporarily relieves cough due to minor throat and bronchial irritation as may occur with a cold
- helps loosen phlegm (mucus) and thin bronchial secretions to drain bronchial tubes

Warnings– Children’s Robitussin Cough & Chest Congestion DM

Do not use

if you are now taking a prescription monoamine oxidase inhibitor (MAOI) (certain drugs for depression, psychiatric, or emotional conditions, or Parkinson’s disease), or for 2 weeks after stopping the MAOI drug. If you do not know if your prescription drug contains an MAOI, ask a doctor or pharmacist before taking this product.

Ask a doctor before use if you have

- cough that occurs with too much phlegm (mucus)
- cough that lasts or is chronic such as occurs with smoking, asthma, chronic bronchitis, or emphysema

Stop use and ask a doctor if

cough lasts more than 7 days, comes back, or is accompanied by fever, rash, or persistent headache.

These could be signs of a serious condition.

If pregnant or breast-feeding,

ask a health professional before use.

Keep out of reach of children.

In case of overdose, get medical help or contact a Poison Control Center right away.

Directions– Children’s Robitussin Cough & Chest Congestion DM

- do not take more than 6 doses in any 24-hour period
- measure only with dosing cup provided
- keep dosing cup with product
- mL = milliliter

age | dose
children under 4 years | do not use
children 4 to under 6 years | 5 mL every 4 hours
children 6 to under 12 years | 10 mL every 4 hours
adults and children 12 years and over | 20 mL every 4 hours

Other information– Children’s Robitussin Cough & Chest Congestion DM

- each 20 mL contains:sodium 21 mg
- store at 20-25°C (68-77°F). Do not refrigerate.

Inactive ingredients– Children’s Robitussin Cough & Chest Congestion DM

anhydrous citric acid, carboxymethylcellulose sodium, FD&C blue no. 1, FD&C red no. 40, glycerin, liquid glucose, natural and artificial flavors, polyethylene glycol, propylene glycol, purified water, sodium benzoate, sodium citrate, sodium gluconate, sucralose, xanthan gum

Questions or comments?– Children’s Robitussin Cough & Chest Congestion DM

call weekdays from 8 AM to 6 PM EST at 1-800-245-1040

Active ingredients (in each 10 mL)– Children’s Robitussin Nighttime Cough Long-Acting DM

Chlorpheniramine maleate, USP 2 mg

Dextromethorphan HBr, USP 15 mg

Purposes –Children’s Robitussin Nighttime Cough Long-Acting DM

Antihistamine

Cough suppressant

Uses –Children’s Robitussin Nighttime Cough Long-Acting DM

- temporarily relieves cough due to minor throat and bronchial irritation as may occur with a cold
- temporarily relieves these symptoms due to hay fever or other upper respiratory allergies:
  - runny nose
  - sneezing
  - itchy, watery eyes
  - itching of the nose or throat

Warnings– Children’s Robitussin Nighttime Cough Long-Acting DM

Do not use

- to sedate a child or to make a child sleepy
- if you are now taking a prescription monoamine oxidase inhibitor (MAOI) (certain drugs for depression, psychiatric, or emotional conditions, or Parkinson’s disease), or for 2 weeks after stopping the MAOI drug. If you do not know if your prescription drug contains an MAOI, ask a doctor or pharmacist before taking this product.

Ask a doctor before use if you have

- trouble urinating due to an enlarged prostate gland
- glaucoma
- a cough that occurs with too much phlegm (mucus)
- a breathing problem or chronic cough that lasts or as occurs with smoking, asthma, chronic bronchitis or emphysema

Ask a doctor or pharmacist before use if you are

taking sedatives or tranquilizers.

When using this product

- do not use more than directed
- marked drowsiness may occur
- avoid alcoholic drinks
- alcohol, sedatives, and tranquilizers may increase drowsiness
- be careful when driving a motor vehicle or operating machinery
- excitability may occur, especially in children

Stop use and ask a doctor if

cough lasts more than 7 days, comes back, or is accompanied by fever, rash, or persistent headache.

These could be signs of a serious condition.

If pregnant or breast-feeding,

ask a health professional before use.

Keep out of reach of children.

In case of overdose, get medical help or contact a Poison Control Center right away.

Directions –Children’s Robitussin Nighttime Cough Long-Acting DM

- measure only with dosing cup provided
- keep dosing cup with product
- mL = milliliter
- do not take more than 4 doses in any 24-hour period

age | dose
children under 6 years | do not use
children 6 to under 12 years | 10 mL every 6 hours
adults and children 12 years and over | 20 mL every 6 hours

Other information –Children’s Robitussin Nighttime Cough Long-Acting DM

- each 10 mL contains:sodium 6 mg
- store at 20-25°C (68-77°F)

Inactive ingredients –Children’s Robitussin Nighttime Cough Long-Acting DM

anhydrous citric acid, FD&C red no. 40, glycerin, lactic acid, natural and artificial flavors, propylene glycol, purified water, sodium benzoate, sodium citrate, sorbitol solution, sucralose

Questions or comments? –Children’s Robitussin Nighttime Cough Long-Acting DM

call weekdays from 8 AM to 6 PM EST at 1-800-245-1040

Additional Information – Children’s Robitussin Day & Night Cough Relief Value Pack

TAMPER-EVIDENT INNER UNITS:

Do Not Use if Tamper-Evident feature on either bottle cap is broken or missing. See individual inner cartons and bottle labels for specific Tamper-Evident features.

Do not take both products within 6 hours of each other.

Children’s Robitussin liquid is specially formulated to provide soothing action, control your child’s cough – plus relieves other cold symptoms.

PARENTS:Learn about teen medicine abuse

www.StopMedicineAbuse.org

Principal Display Panel – Children’s Robitussin Day & Night Cough Relief Value Pack

DAY & NIGHT

COUGH RELIEF

VALUE PACK

Children’s Robitussin

AGES 4 & OVER

Cough & Chest Congestion DM

DEXTROMETHORPHAN HBr

(Cough Suppressant)

GUAIFENESIN

(Expectorant)

Relieves:

- Chest Congestion/Mucus
- Cough

grapeflavor

4 FL OZ (118 mL)

AGES 6 & OVER

Nighttime Cough Long-Acting DM

CHLORPHENIRAMINE MALEATE

(Antihistamine)

DEXTROMETHORPHAN HBr (Cough Suppressant)

Relieves:

- Cough Up to 8 Hours
- Runny Nose

Alcohol-free

fruit punchflavor

4 FL OZ (118 mL)

Principal Display Panel – Children’s Robitussin Cough & Chest Congestion DM

Children’s

Robitussin

FOR AGES 4 & OVER

Cough & Chest Congestion DM

DEXTROMETHORPHAN HBr
(Cough Suppressant)

GUAIFENESIN
(Expectorant)

Relieves:

- Chest Congestion/Mucus
- Cough

BETTER TASTING!*

Great Grape Taste

grapeflavor

4 FL OZ (118 mL)

Principal Display Panel – Children’s Robitussin Nighttim e Cough DM

Children’s

Robitussin

AGES 6 & OVER

Nighttime Cough DM

Long-Acting

CHLORPHENIRAMINE MALEATE
(Antihistamine)

DEXTROMETHORPHAN HBr
(Cough Suppressant)

Relieves:

- Cough Up to 8 Hours
- Runny Nose

Alcohol-Free

fruit punchflavor

4 FL OZ (118 mL)